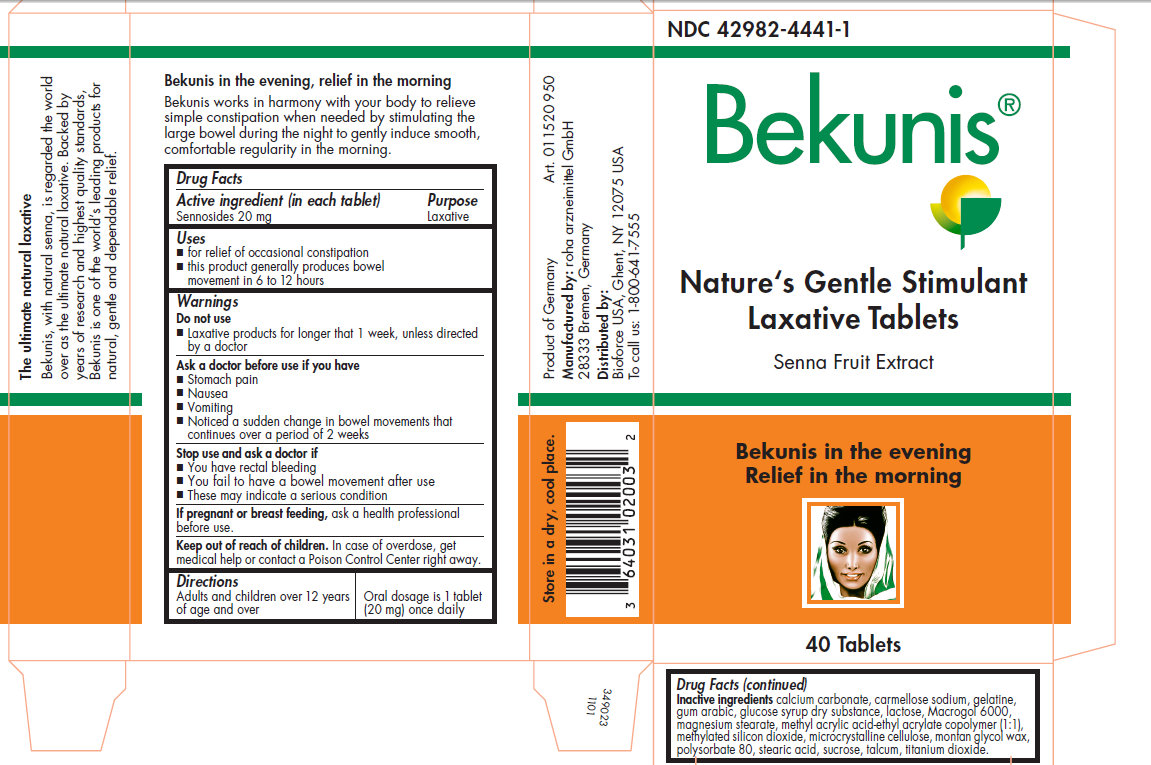 DRUG LABEL: Bekunis Natures Gentle Stimulant Laxative
NDC: 42982-4441 | Form: TABLET, SUGAR COATED
Manufacturer: roha arzneimittel GmbH
Category: otc | Type: HUMAN OTC DRUG LABEL
Date: 20110213

ACTIVE INGREDIENTS: SENNOSIDES A AND B 20 mg/1 1
INACTIVE INGREDIENTS: CALCIUM CARBONATE; CARBOXYMETHYLCELLULOSE SODIUM; GELATIN; ACACIA; DEXTROSE; LACTOSE; MAGNESIUM STEARATE; CELLULOSE, MICROCRYSTALLINE; POLYSORBATE 80; STEARIC ACID; SUCROSE; TITANIUM DIOXIDE

Bekunis Nature's Gentle Stimulant Laxative Tablets

The ultimate natural laxative

Bekunis, with natural senna, is regarded the world over as the ultimate natural laxative. Backed by years of research and highest quality standards, Bekunis is one of the world's leading products for natural, gentle and dependable relief.

Bekunis in the evening, relief in the morning

Bekunis works in harmony with your body to relieve simple constipation when needed by stimulating the large bowel during the night to gently induce smooth, comfortable regularity in the morning.

Drug Facts

Active ingredient (in each tablet)

Sennosides 20 mg

Purpose

Laxative

Uses

- for relief of occasional constipation
- this product generally produces bowel movement in 6 to 12 hours

Warnings

Do not use

- Laxative products for longer that 1 week, unless directed by a doctor.

Ask a doctor before use if you have

- Stomach pain
- Nausea
- Vomiting
- Noticed a sudden change in bowel movements that continues over a period of 2 weeks

Stop use and ask a doctor if

- You have rectal bleeding
- You fail to have a bowel movement after use
- These may indicate a serious condition

PREGNANCY OR BREAST FEEDING

If pregnant or breast feeding, ask a health professional before use.

Keep out of reach of children. In case of overdose, get medical help or contact a Poison Control Center right away.

Directions

Adults and children over 12 years of age and over | Oral Dosage is 1 tablet (20 mg) once daily

Product of Germany

Manufactured by: roha arzneimittel GmbH 28333 Bremen, Germany

Distributed by: Bioforce USA, Ghent, NY 12075 USA

To call us: 1-800-641-7555

STORAGE AND HANDLING

Store in a dry, cool place.

INACTIVE INGREDIENT

Inactive ingredients calcium carbonate, carmellose sodium, gelatine, gum arabic, glucose syrup dry substance, lactose, Macrogol 6000, magnesium stearate, methyl acrylic acid-ethyl acrylate copolymer (1:1), methylated silicon dioxide, microcrystalline celluclose, montan glycol wax, polysorbate 80, stearic acid, sucrose, talcum, titanium dioxide.

PACKAGE LABEL

NDC 42982-4441-1

Bekunis

Nature's Gentle Stimulant

Laxative Tablets

Senna Fruit Extract

Bekunis in the evening

Relief in the morning

40 Tablets